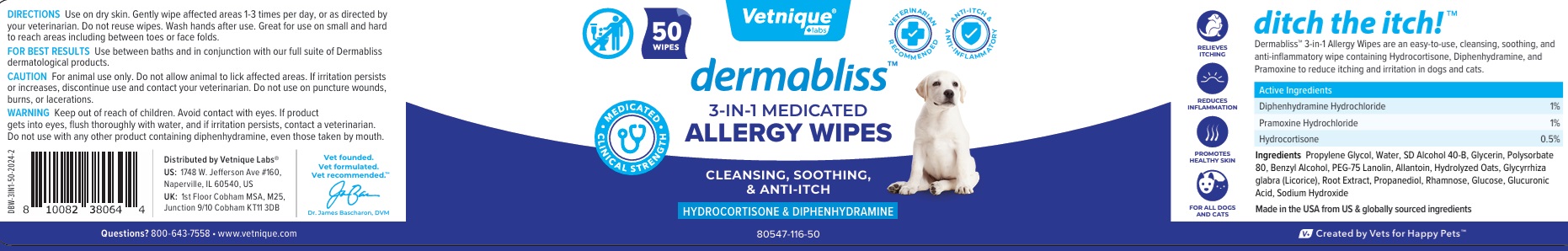 DRUG LABEL: Dermabliss 3-IN-1 MEDICATED ALLERGY WIPES
NDC: 80547-116 | Form: CLOTH
Manufacturer: Vetnique Labs Llc
Category: animal | Type: OTC ANIMAL DRUG LABEL
Date: 20241026

ACTIVE INGREDIENTS: DIPHENHYDRAMINE HYDROCHLORIDE 10 mg/1 mL; PRAMOXINE HYDROCHLORIDE 10 mg/1 mL; HYDROCORTISONE 5 mg/1 mL
INACTIVE INGREDIENTS: PROPYLENE GLYCOL; WATER; ALCOHOL; GLYCERIN; POLYSORBATE 80; BENZYL ALCOHOL; PEG-75 LANOLIN; ALLANTOIN; OAT; GLYCYRRHIZA GLABRA; PROPANEDIOL; RHAMNOSE; ANHYDROUS DEXTROSE; GLUCURONIC ACID; SODIUM HYDROXIDE

dermabliss™ 3-IN-1 MEDICATED ALLERGY WIPES

Active Ingredients

Diphenhydramine Hydrochloride 1%
Pramoxine Hydrochloride 1%
Hydrocortisone 0.5%

PURPOSE

ANTI-ITCH

INDICATIONS AND USAGE

Dermabliss™ 3-in-1 Allergy Wipes are an easy-to-use, cleansing, soothing, and anti-inflammatory wipe containing Hydrocortisone, Diphenhydramine, and Pramoxine to reduce itching and irritation in dogs and cats.

Ingredients

Propylene Glycol, Water, SD Alcohol 40-B, Glycerin, Polysorbate 80, Benzyl Alcohol, PEG-75 Lanolin, Allantoin, Hydrolyzed Oats, Glycyrrhiza glabra (Licorice), Root Extract, Propanediol, Rhamnose, Glucose, Glucuronic Acid, Sodium Hydroxide

DIRECTIONS

Use on dry skin. Gently wipe affected areas 1-3 times per day, or as directed by your veterinarian. Do not reuse wipes. Wash hands after use.
Great for use on small and hard to reach areas including between toes or face folds.

FOR BEST RESULTS: Use between baths and in conjunction with our full suite of Dermabliss dermatological products.

CAUTION

For animal use only. Do not allow animal to lick affected areas. If irritation persists or increases, discontinue use and contact your veterinarian.
Do not use on puncture wounds, burns, or lacerations.

WARNING

Keep out of reach of children. Avoid contact with eyes. If product gets into eyes, flush thoroughly with water, and if irritation persists, contact a veterinarian. Do not use with any other product containing diphenhydramine, even those taken by mouth.

• MEDICATED • CLINICAL STRENGTH

VETERINARIAN RECOMMENDED

ANTI-ITCH & ANTI-INFLAMMATORY

CLEANSING, SOOTHING, & ANTI-ITCH

RELIEVES ITCHING

REDUCES INFLAMMATION

PROMOTES HEALTHY SKIN

FOR ALL DOGS AND CATS

ditch the itch!™

Made in the USA from US & globally sourced ingredients

V+ Created by Vets for Happy Pets™

Distributed by Vetnique Labs®

US: 1748 W. Jefferson Ave #160,
Naperville, IL 60540, US

UK: 1st Floor Cobham MSA, M25,
Junction 9/10 Cobham KT11 3DB

Vet founded.
Vet formulated.
Vet recommended.™

Questions? 800-643-7558 • www.vetnique.com